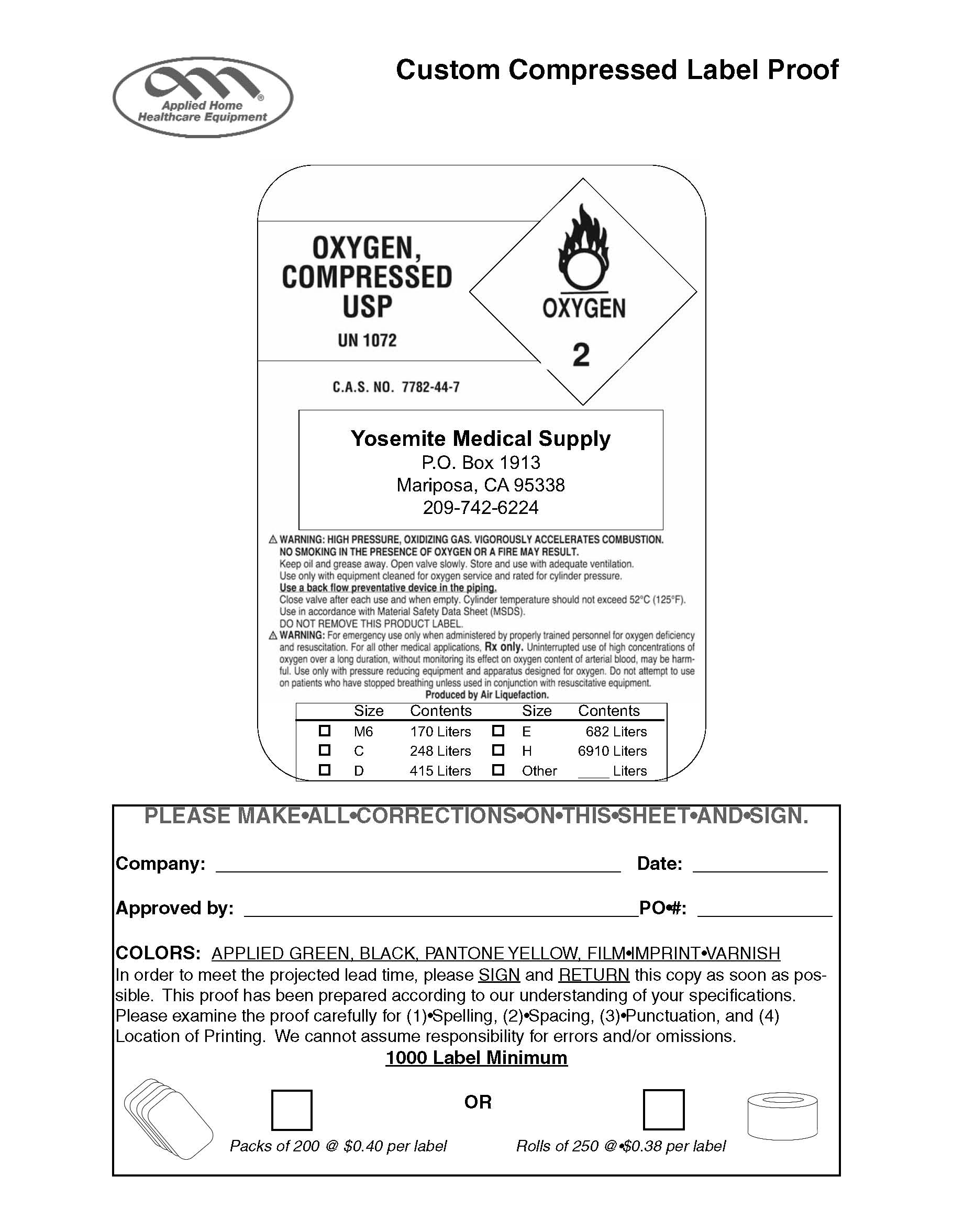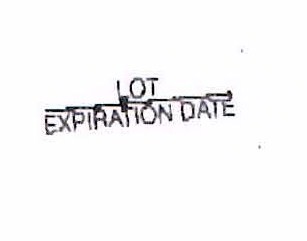 DRUG LABEL: Oxygen
NDC: 39338-1072 | Form: GAS
Manufacturer: Yosemite Medical Supply
Category: prescription | Type: HUMAN PRESCRIPTION DRUG LABEL
Date: 20100114

ACTIVE INGREDIENTS: Oxygen 99 L/100 L

Oxygen